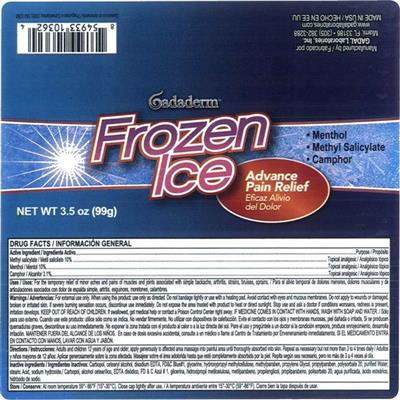 DRUG LABEL: GADADERM Frozen Ice Advance Pain Relief
NDC: 53113-362 | Form: GEL
Manufacturer: GADAL Laboratories, Inc
Category: otc | Type: HUMAN OTC DRUG LABEL
Date: 20161118

ACTIVE INGREDIENTS: METHYL SALICYLATE 10 1/100 g; MENTHOL 10 1/100 g; CAMPHOR (NATURAL) 3.1 1/100 g
INACTIVE INGREDIENTS: CARBOXYPOLYMETHYLENE; PROPYLENE GLYCOL; CETOSTEARYL ALCOHOL; EDETATE DISODIUM ANHYDROUS; FD&C BLUE NO. 1; GLYCERIN; HYPROMELLOSE, UNSPECIFIED; METHYLPARABEN; PROPYLPARABEN; POLYSORBATE 20; WATER; STEARIC ACID; SODIUM HYDROXIDE

ACTIVE INGREDIENTS

Active Ingredients | Purpose
Methyl Salicylate 10% | Topical Analgesic
Menthol 10% | Topical Analgesic
Camphor 3.1% | Topical Analgesic

INACTIVE INGREDIENT

Carbopol, Cetearyl Alcohol, Disodium EDTA, FD&C Blue #1, Glycerin, Hydroxypropyl Methylcellulose, Menthylparaben, Propylene Glycol, Propylparaben, Polysorbate 20, Purified Water, Stearic Acid, Sodium Hydroxide.

WARNINGS

For the external use only. When using this product use as directed.

- Do not bandage tightly or use with heating pad. Avoid contact with eyes and mucous membranes.
- Do not apply to wounds or damaged, broken, or irritated skin.
- If severe burning sensation occurs, discontinue use immediately.
- Do not expose the area treated with product to heat or direct sunlight.
- Stop use and ask a doctor if conditions worsen, redness is present, irritation develops.

If swallowed, get medical help or contact a Poison Control Center right away. IF MEDICINE COMES IN CONTACT WITH HANDS, WASH WITH SOAP AND WATER.

DOSAGE & ADMINISTRATION

Adults and children 12 years of age and older; apply generously to affected area massage into painful area until thoroughly absorbed into skin. Repeat as necessary but not more than 3 to 4 times daily.

PURPOSE

For temporary relief of minor aches and pains of muscles and joints associated with simple backache, arthritis, strains, bruises, sprains.